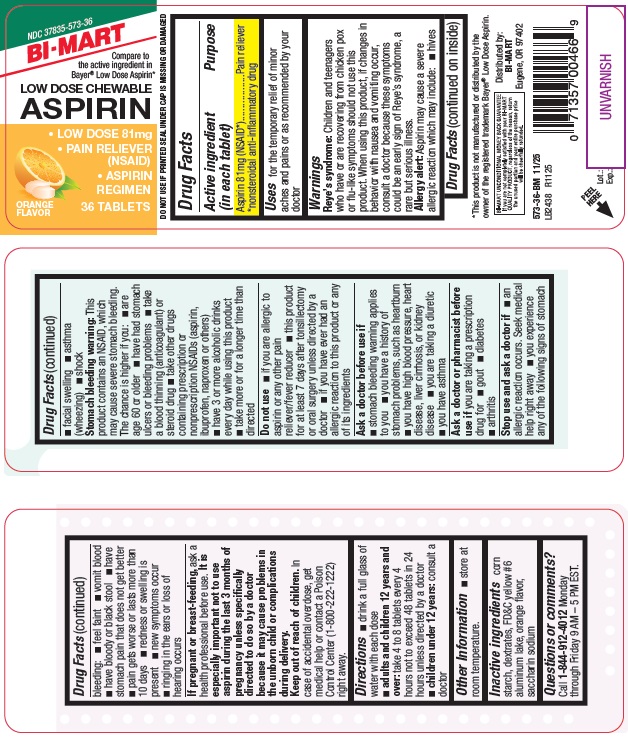 DRUG LABEL: Low Dose Chewable Aspirin
NDC: 37835-573 | Form: TABLET, CHEWABLE
Manufacturer: Bi-Mart
Category: otc | Type: HUMAN OTC DRUG LABEL
Date: 20251001

ACTIVE INGREDIENTS: ASPIRIN 81 mg/1 1
INACTIVE INGREDIENTS: STARCH, CORN; DEXTRATES; FD&C YELLOW NO. 6; SACCHARIN SODIUM

Low Dose Chewable Aspirin

Active ingredient (in each tablet)

Aspirin 81 mg (NSAID*)

*nonsteroidal anti-inflammatory drug

Purpose

Pain reliever

Uses

- for the temporary relief of minor aches and pains or as recommended by your doctor

Warnings

Reye's syndrome:Children and teenagers who have or are recovering from chicken pox or flu-like symptoms should not use this product. When using this product, if changes in behavior with nausea and vomiting occur, consult a doctor because these symptoms could be an early sign of Reye's syndrome, a rare but serious illness.

Allergy Allert:Aspirin may cause a severe allergic reaction which may include:

- hives
- facial swelling
- asthma (wheezing)
- shock

Stomach bleeding warning:This product contains an NSAID, which may cause severe stomach bleeding. The chance is higher if you:

- are age 60 or older
- have had stomach ulcers or bleeding problems
- take a blood thinning (anticoagulant) or steroid drug
- take other drugs containing prescription or nonprescription NSAIDs (aspirin, ibuprofen, naproxen, or others)
- have 3 or more alcoholic drinks every day while using this product
- take more or for a longer time than directed

Do not use

- if you are allergic to aspirin or any other pain reliever/fever reducer
- this product for at least 7 days after tonsillectomy or oral surgery unless directed by a doctor
- If you have ever had an allergic reaction to this product or any of its ingredients

Ask a doctor before use if

- stomach bleeding warning applies to you
- you have a history of stomach problems, such as heartburn
- you have high blood pressure, heart disease, liver cirrhosis, or kidney disease
- you are taking a diuretic
- you have asthma

Ask a doctor or pharmacist before use if

you are taking a prescription drug for

- gout
- diabetes
- arthritis

Stop use and ask a doctor if

- an allergic reaction occurs. Seek medical help right away
- you experience any of the following signs of stomach bleeding:

• feel faint
• vomit blood
• have bloody or black stool
• have stomach pain that does not get better
• pain gets worse or last mote than 10 days
• readness or swelling is present
• new symptoms occur
• ringing in the ears or loss of hearing occurs

If pregnant or breast-feeding,

ask a health professional before use. It is especially important not to use aspirin during the last 3 months of pregnancy unless specifically directed to do so by a doctor because it may cause problems in the unborn child or complications during delivery.

Keep out of reach of children.

In case of accidental overdose, get medical help or contact a Poison Control Center (1-800-222-1222) right away.

Directions

- drink a full glass of water with each dose
- adults and children 12 years and over: take 4 to 8 tablets every 4 hours not to exceed 48 tablets in 24 hours unless directed by a doctor
- children under 12 years:consult a doctor

Other information

- store at room temperature

Inactive ingredients

corn starch, dextrates, FD&C yellow #6 aluminum lake, orange flavor, saccharin sodium

Questions or comments?

Call 1-844-912-4012 Monday through Friday 9 AM - 5 PM EST.